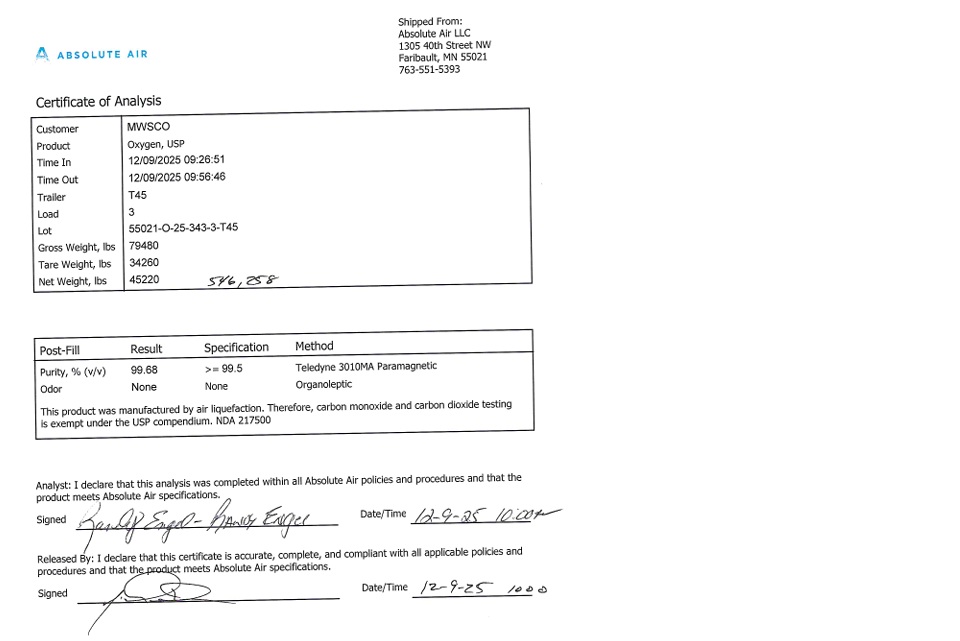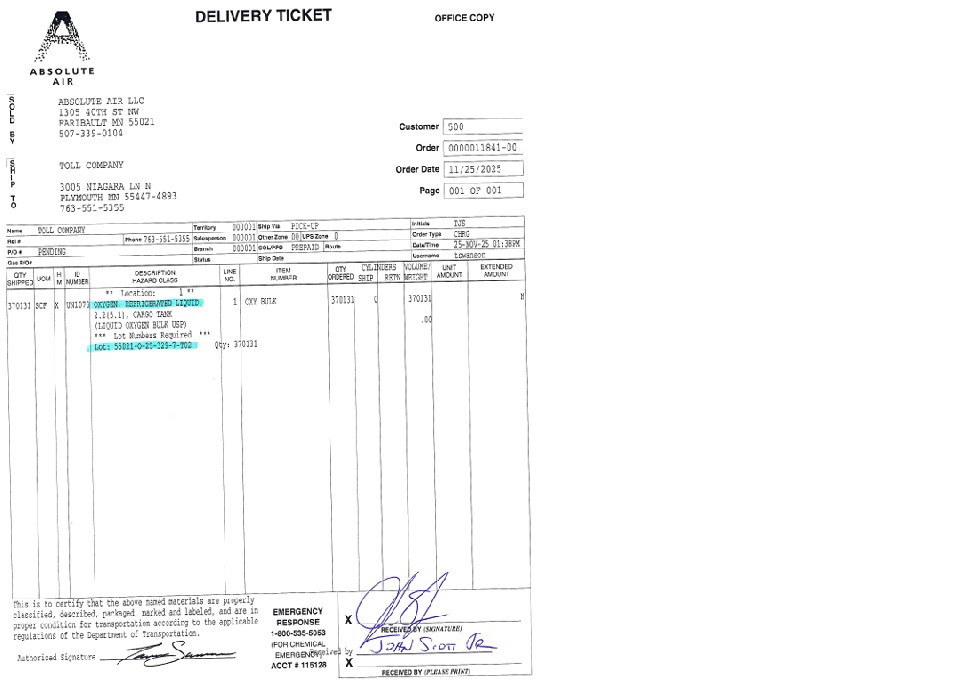 DRUG LABEL: Oxygen
NDC: 82666-001 | Form: GAS
Manufacturer: ABSOLUTE AIR LLC
Category: prescription | Type: HUMAN PRESCRIPTION DRUG LABEL
Date: 20251216

ACTIVE INGREDIENTS: OXYGEN 995 mL/1 L

Oxygen

PACKAGE LABEL

ABSOLUTE AIR

Shipped From:

Absolute Air LLC

1305 40th Street NW

Faribault, MN 55021

763-551-5393

Certificate of Analysis

Customer TOLL

Product Oxygen, USP

Time In 11/25/2025 13:10:12

Time Out 11/25/2025 13:37:49

Trailer T02

Load 7

Lot 55021-O-25-329-7-T02

Gross Weight, lbs 79500

Tare Weight, lbs 48860

Net Weight, lbs 30640

Post-Fill Result Specification Method

Purity, % (v/v) 99.74 > = 99.5 Teledyne 3010MA Paramagnetic

Odor None None Organoleptic

This product was manufactured by air liquefaction. Therefore, carbon monoxide and carbon dioxide testing is exempt under the USP compendium. NDA 217500

Analyst: I declare that this analysis was completed within all Absolute Air policies and procedures and that the produce meets Absolute Air specifications.

Signed Date/Time

Released By: I declare that this certificate is accurate, complete, and compliant with all applicable policies and procedures and that the product meets Absolute Air specifications.

Signed Date/Tim

Warning: For emergency use only when administered by properly trained personnel for oxygen deficiency and resuscitation. For all other Medical applications, Rx required.

No smoking or vaping. Keep away from open flame.

Produced by air liquefaction.

PACKAGE LABEL

ABSOLUTE AIR DELIVERY TICKEY OFFICE COPY

SOLD BY

ABSOLUTE AIR LLC

1305 40TH ST NW

FARIBAULT, MN 55021

507-339-0104

SHIP TO

TOLL COMPANY

3005 NIAGARA LN N

PLYMOUTH, MN 55447-4893

763-551-5355

Customer 500

Order 0000011841-00

Order Date 11/25/2025

Page 001 OF 001

Name TOLL COMPANY Territory 000001 Ship Via PICK-UP Initials TJS

Ref # Phone 763-551-5355 Salesperson 000001 Other Zone 00 UPS Zone 0 Order Type CHRG

P/O# PENDING Branch 000001 COL/PPD PREPAID Route Date/Time 25-Nov-25 01:38PM

Gas P/O# Status Ship Date Username tswanson

QTY SHIPPED UOM HM ID NUMBER Description HAZARD CLASS LINE NO. ITEM NUMBER QTY ORDERED CYLINDERS SHIP RETN VOLUME/WEIGHT UNIT AMOUNT EXTENDED AMOUNT

370131 SCF X UN1073 **Location: 1** OXYGEN, REFRIGERATED LIQUID, 2.2 (5.1), CARGO TANK (LIQUID OXYGEN BULK USP) ***Lot Numbers Required*** Lot: 55021-O-25-329-7-T02 1 Qty: 370131 OXY BULK 370131 0 370131 .00 N

This is to certify that the above named materials are properly classified, described, packaged, marked and labeled, and are in proper condition for transportation according to the applicable regulations of the Department of Transportation.

Authorized Signature

EMERGENCY RESPONSE 1-800-535-5053 (FOR CHEMICAL EMERGENCY)

ACCT # 115128

X RECEIVED BY (SIGNATURE)

X RECEIVED BY (PLEASE PRINT)